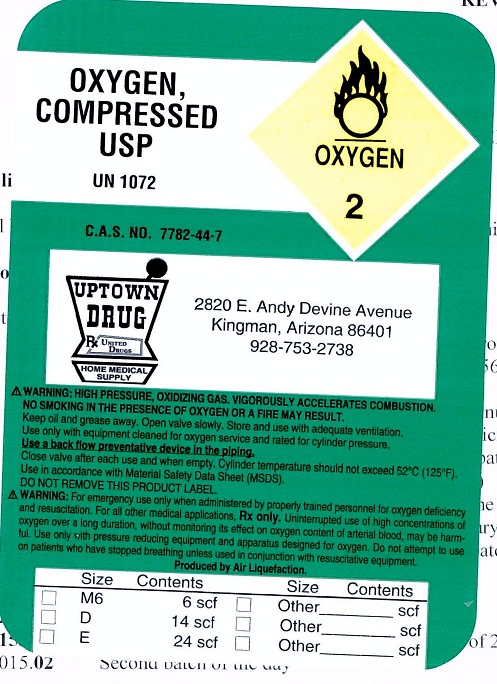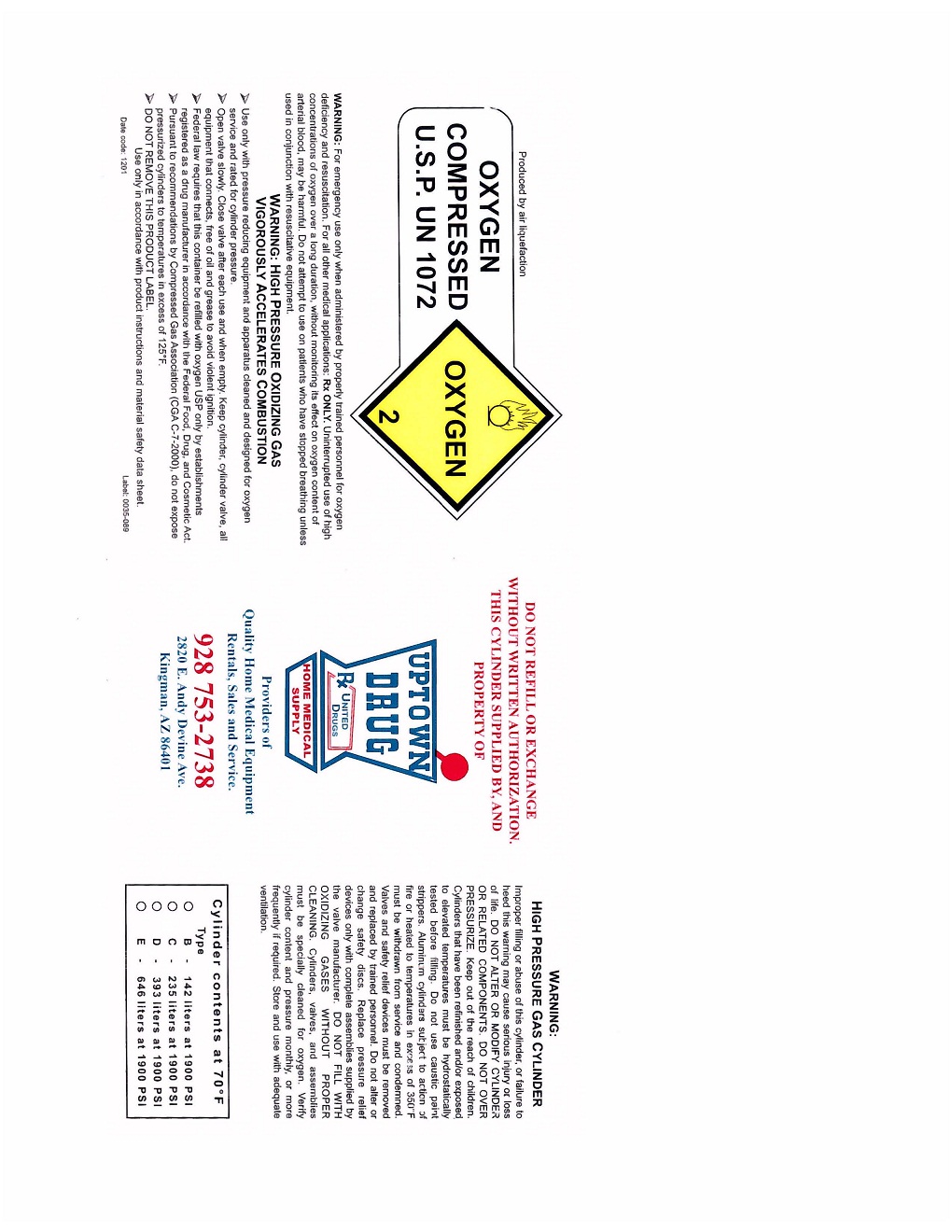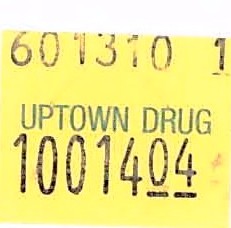 DRUG LABEL: Oxygen
NDC: 35567-0001 | Form: GAS
Manufacturer: Uptown Pharmacy of Kingsman
Category: prescription | Type: HUMAN PRESCRIPTION DRUG LABEL
Date: 20100218

ACTIVE INGREDIENTS: Oxygen 99 L/100 L

Oxygen